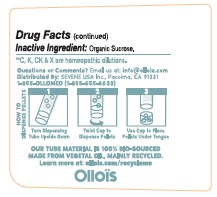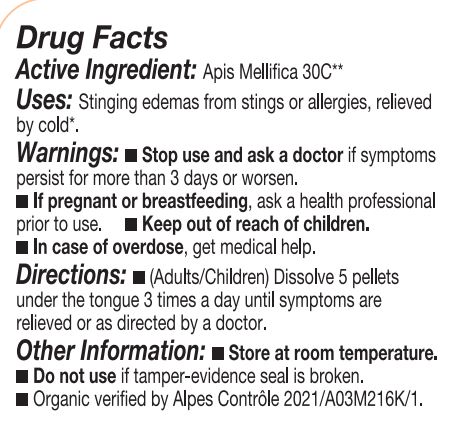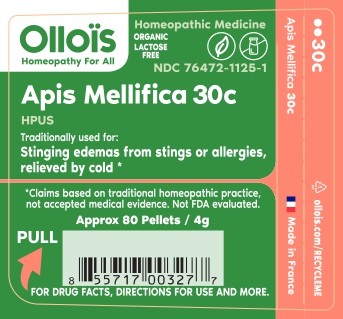 DRUG LABEL: APIS MELLIFERA
NDC: 76472-1125 | Form: PELLET
Manufacturer: SEVENE USA
Category: homeopathic | Type: HUMAN OTC DRUG LABEL
Date: 20250522

ACTIVE INGREDIENTS: APIS MELLIFERA 30 [hp_C]/1 1
INACTIVE INGREDIENTS: SUCROSE

Sevene USA (as PLD) - APIS MELLIFICA 30C (76472-1125)

ACTIVE INGREDIENT

HOMEOPATHIC DILUTION OF HPUS Apis Mellifica 30C.

TRADITIONALLY USED FOR

Stinging edemas from stings or allergies, relieved by cold*

DIRECTIONS

(adults/children) Dissolve 5 pellets under the tongue 3 times a day until symptoms are relieved or as directed by a physician.

USE

Condition listed above or as directed by a physician.

WARNINGS

Stop use and ask a physician if symptoms persist for more than 3 days or worsen.

PREGNANCY OR BREAST FEEDING

If pregnant or breast-feeding, ask a health professional before use.

Keep out of reach of children.

OTHER INFORMATION

Store at room temperature.

Do not use if pellet-dispenser seal is broken.

INACTIVE INGREDIENT

Sucrose.

QUESTIONS?

INFO@OLLOIS.COM * www.ollois.com * MADE IN FRANCE. NOT REVIEWED BY THE FDA AND NOT GUARANTEED TO BE EFFECTIVE. THIS HOMEOPATHIC DILUTION MAY NOT BE SUSCEPTIBLE TO SCIENTIFIC MEASUREMENT.